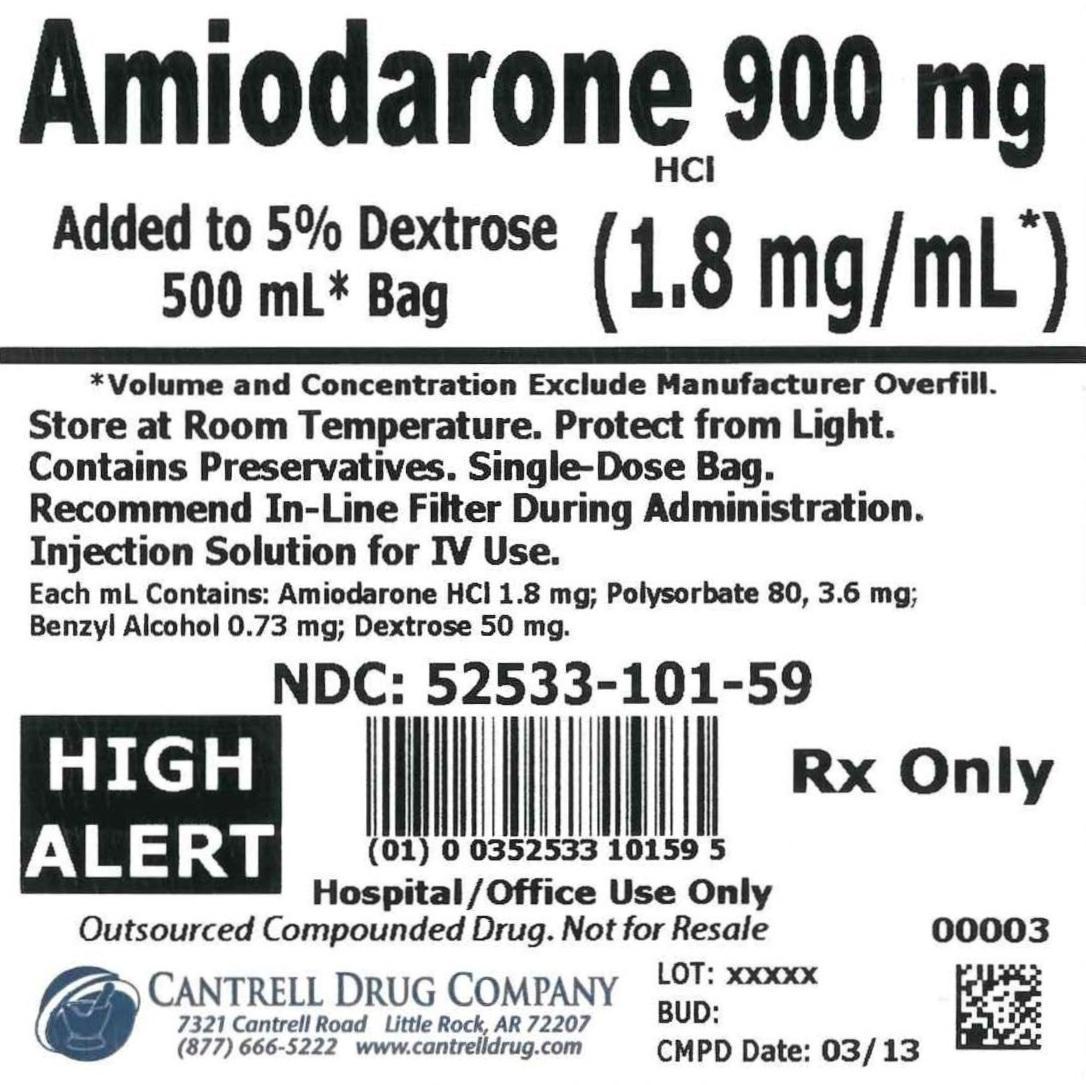 DRUG LABEL: Amiodarone HCl
NDC: 52533-101 | Form: INJECTION, SOLUTION
Manufacturer: Cantrell Drug Company
Category: prescription | Type: HUMAN PRESCRIPTION DRUG LABEL
Date: 20140820

ACTIVE INGREDIENTS: AMIODARONE HYDROCHLORIDE 1.8 mg/1 mL
INACTIVE INGREDIENTS: Dextrose 50 mg/1 mL; POLYSORBATE 80 3.6 mg/1 mL; BENZYL ALCOHOL 0.73 mg/1 mL; WATER

Amiodarone HCl 900 mg Added to 5% Dextrose 500 mL Bag